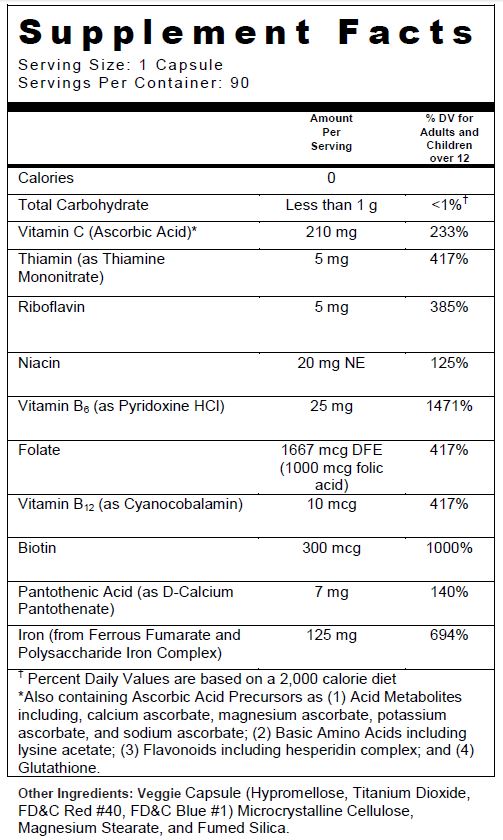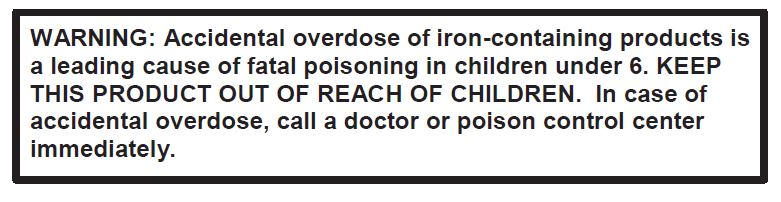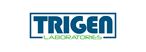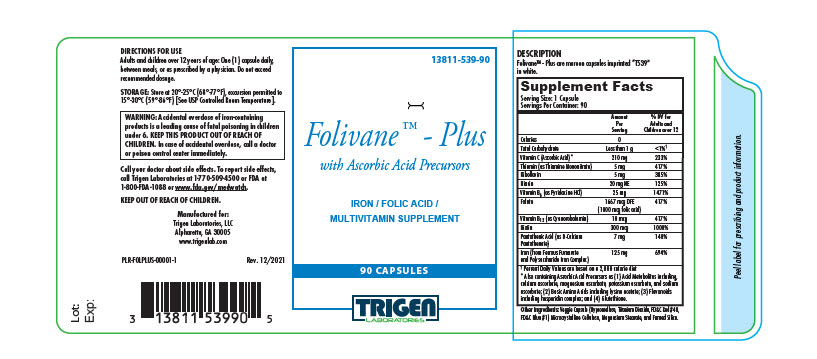 DRUG LABEL: Folivane-Plus with Ascorbic Acid Precursors
NDC: 13811-539 | Form: CAPSULE
Manufacturer: Trigen Laboratories, LLC
Category: other | Type: DIETARY SUPPLEMENT
Date: 20220107

ACTIVE INGREDIENTS: FERROUS FUMARATE 62.5 mg/1 1; IRON 62.5 mg/1 1; ASCORBIC ACID 210 mg/1 1; THIAMINE MONONITRATE 5 mg/1 1; RIBOFLAVIN 5 mg/1 1; NIACIN 20 mg/1 1; PYRIDOXINE HYDROCHLORIDE 25 mg/1 1; FOLIC ACID 1 mg/1 1; CYANOCOBALAMIN 10 ug/1 1; BIOTIN 300 ug/1 1; CALCIUM PANTOTHENATE 7 mg/1 1
INACTIVE INGREDIENTS: HYPROMELLOSES; TITANIUM DIOXIDE; FD&C RED NO. 40; FD&C BLUE NO. 1; MICROCRYSTALLINE CELLULOSE; MAGNESIUM STEARATE; SILICON DIOXIDE

Folivane-Plus with Ascorbic Acid Precursors

SUPPLEMENT FACTS

Folivane™ - Plus is a prescription multivitamin nutritional supplement indicated for improving nutritional status in adults with certainty illnesses or vitamin deficiencies. DO NOT ADMINISTER TO CHILDREN UNDER THE AGE OF 12.

CONTRAINDICATIONS

Folivane™ - Plus is contraindicated in patients with known hypersensitivity to any of its ingredients; also, all iron compounds are contraindicated in patients with hemosiderosis, hemochromatosis, or hemolytic anemias. Pernicious anemia is a contraindication, as folic acid may obscure its signs and symptoms.

PRECAUTIONS

General: Folic acid alone is improper therapy in the treatment of pernicious anemia and other megaloblastic anemias where B12 is deficient. Folic acid in doses above 0.1 mg daily may obscure pernicious anemia assessment, such that hematologic remission can occur while neurological manifestations remain progressive.

Biotin levels higher than the recommended daily allowance may cause interference with some laboratory tests, including lead to incorrect test results. Tell your healthcare provider about all prescription and over-the-counter medicines, vitamins, and dietary supplements that you take, including biotin.

Pediatric Use: Safety and effectiveness of this product have not been established in pediatric patients.

Geriatric Use: Safety and effectiveness of this product have not been established in elderly patients.

DRUG INTERACTIONS

Folivane™ - Plus is not recommended for and should not be given to patients receiving levodopa because the action of levodopa is antagonized by pyridoxine. There is a possibility of increased bleeding due to pyridoxine interaction with anticoagulants (e.g. Aspirin, Heparin, Clopidogrel).

ADVERSE REACTIONS

Folic Acid: Allergic sensitizations have been reported following both oral and parenteral administration of folic acid.

Ferrous Fumarate: Gastrointestinal disturbances (anorexia, nausea, diarrhea, constipation) occur occasionally, but are usually mild and may subside with continuation of therapy. Although the absorption of iron is best when taken between meals, taking Folivane™ - Plus after meals may diminish occasional G.I. disturbances. Folivane™ - Plus is best absorbed when taken at bedtime.

OVERDOSAGE

Acute overdosage of iron may cause abdominal pain, nausea and vomiting and, in severe cases, cardiovascular collapse and death. Other more chronic symptoms include pallor and cyanosis, melena, shock, drowsiness and coma. The estimated overdose of orally ingested iron is 300 mg/kg body weight. Toxic effects are seen at 10-20 mg/kg elemental iron. When overdoses are ingested by children, severe reactions, including fatalities, have resulted. Folivane™-Plus should be stored beyond the reach of children to prevent against accidental iron poisoning. Keep this product out of the reach of children.

Treatment: For specific therapy, exchange transfusion and chelating agents should be used. For general management, perform gastric lavage with sodium bicarbonate solution or milk. Administer intravenous fluids and electrolytes and use oxygen.

DESCRIPTION

Folivane™ - Plus are maroon capsules imprinted “T539” in white.

DIRECTIONS FOR USE

Adults and children over 12 years of age: One (1) capsule daily, between meals, or as prescribed by a physician. Do not exceed recommended dosage.

HOW SUPPLIED

Folivane™ - Plus is dispensed in child-resistant bottles of 90 capsules.

Product Code: 13811-539-90

STORAGE

Store at 20°-25°C (68°-77°F), excursions permitted to 15°-30°C (59°-86°F) [See USP Controlled Room Temperature].

KEEP OUT OF REACH OF CHILDREN.

For use on the order of a healthcare practitioner.

Call your doctor about side effects. To report side effects, call Trigen Laboratories at 1-770-509-4500 or FDA at 1-800-FDA-1088 or www.fda.gov/medwatch.

PLR-FOLPLUS-00001-1 Rev. 12/2021

Manufactured For:
Trigen Laboratories, LLC
Alpharetta, GA 30005

PRINCIPAL DISPLAY PANEL

Folivane-Plus with Ascorbic Acid Precursors 90ct

13811-539-90